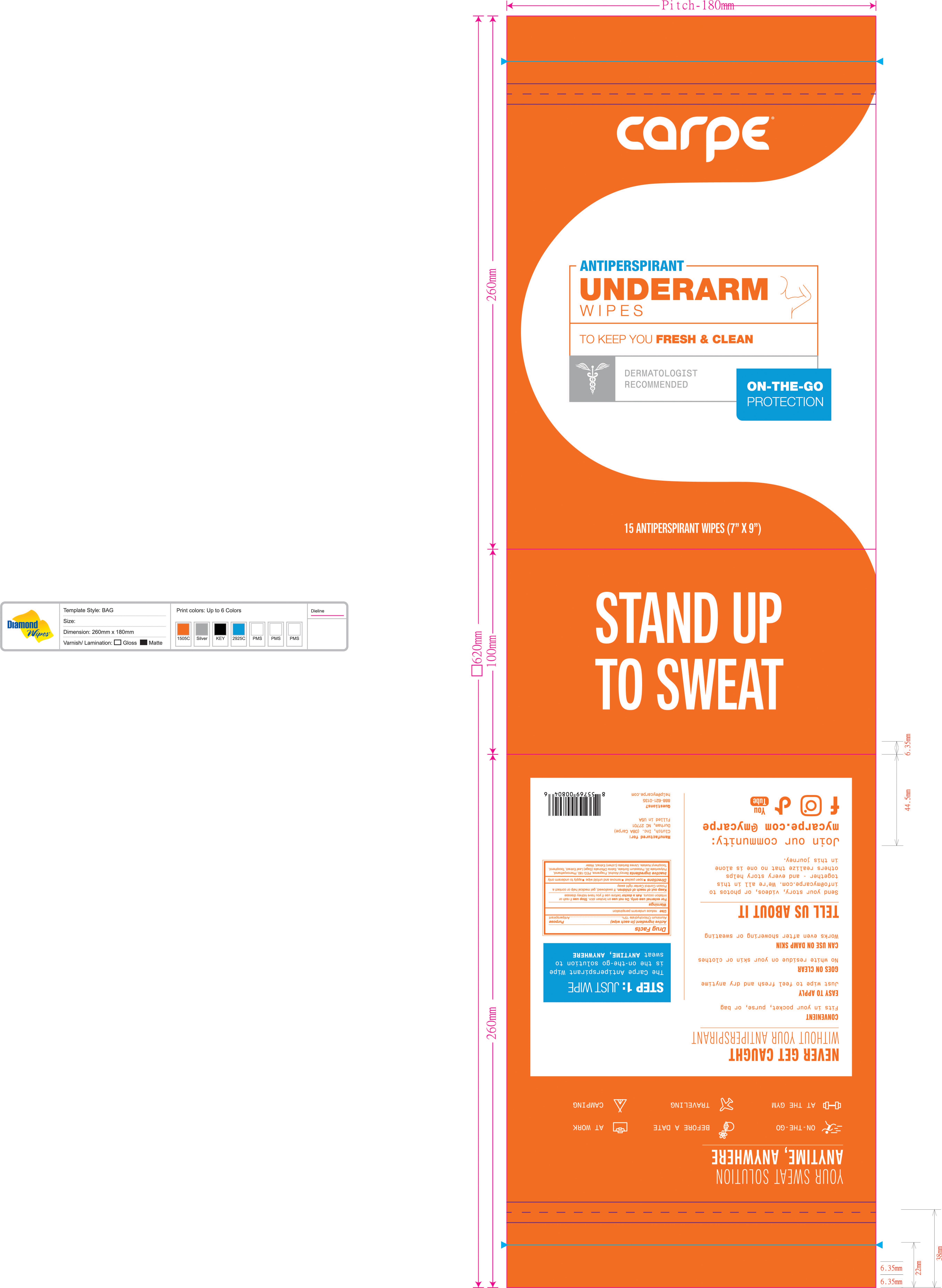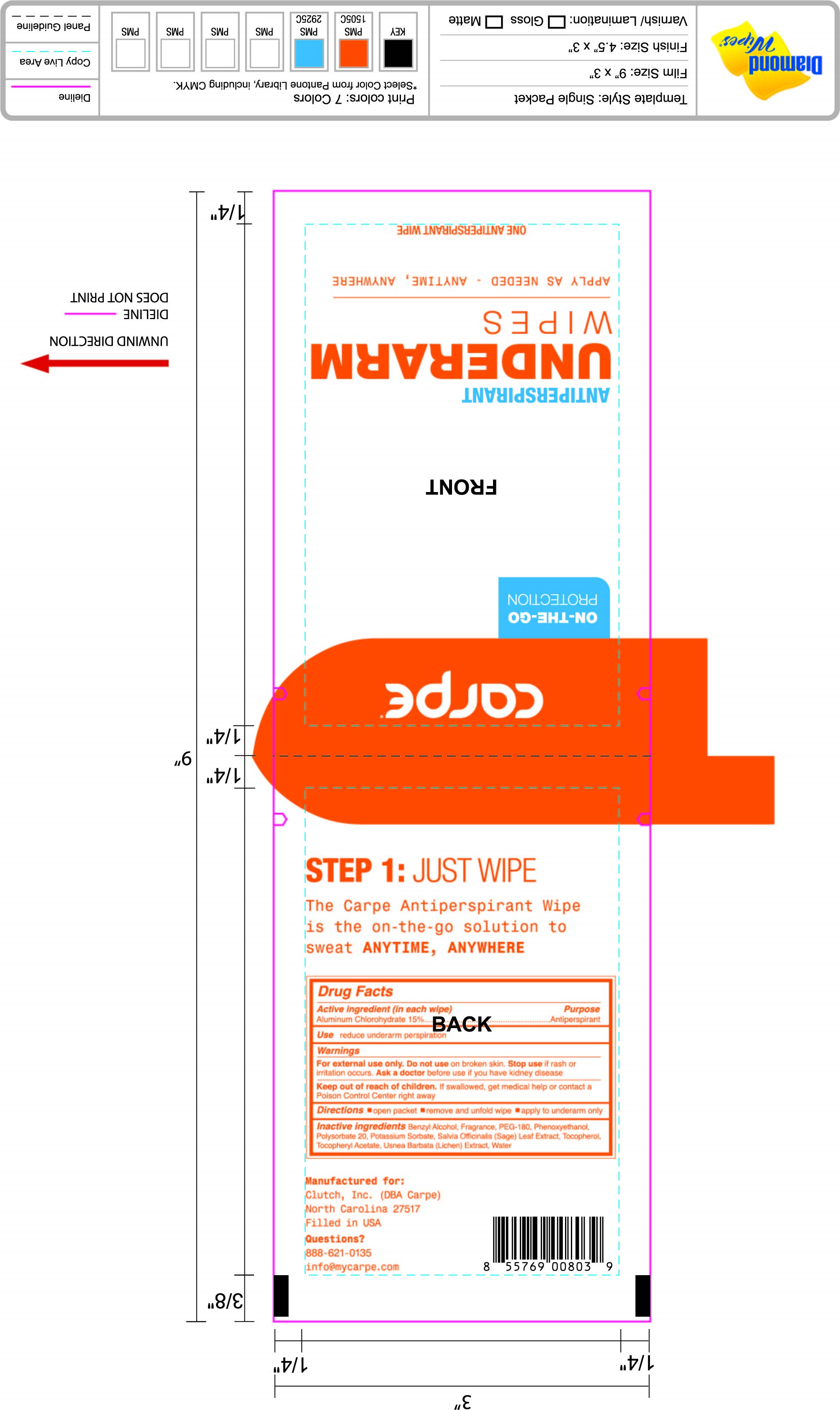 DRUG LABEL: On-the-go Underarm Antiperspirant  Wipes
NDC: 74307-011 | Form: SOLUTION
Manufacturer: Clutch Inc
Category: otc | Type: HUMAN OTC DRUG LABEL
Date: 20251211

ACTIVE INGREDIENTS: ALUMINUM CHLOROHYDRATE 15 g/100 g
INACTIVE INGREDIENTS: .ALPHA.-TOCOPHEROL ACETATE; WATER; TOCOPHEROL; SAGE; USNEA BARBATA; POLYSORBATE 20; PHENOXYETHANOL; POTASSIUM SORBATE; BENZYL ALCOHOL; POLYETHYLENE GLYCOL 8000

On-the-go Underarm Antiperspirant Wipes

Active Ingredients (In each Wipe) Purpose

Aluminum Chlorohydrate 15% Antiperspirant

PURPOSE

Usereduce underarm perspiration

Keep out of reach of children.If swallowed, get medical help or contact a Poison Control Center

INDICATIONS AND USAGE

Stop useif rash or irritation occurs.

Warnings

For external use only. Do not useon broken skin.

Ask a doctorbefore use if you have kidney disease

Directions

- open packet
- remove and unfold wipe
- apply to underarm only

INACTIVE INGREDIENT

Inactive IngredientsBenzyl Alcohol, Fragrance, PEG-180, Phenoxyethanol, Polysorbate 20, Potassium Sorbate, Salvia Officinalis (Sage) Leaf Extract, Tocopheryl Acetate, Usnea Barbata (Lichen) Extract, Water

PACKAGE LABEL

carpe

Antiperspirant

underarm wipes

To keep you fresh & Clean

On-The- Go Protection

15 Antiperspirant wipes (7" X 9")